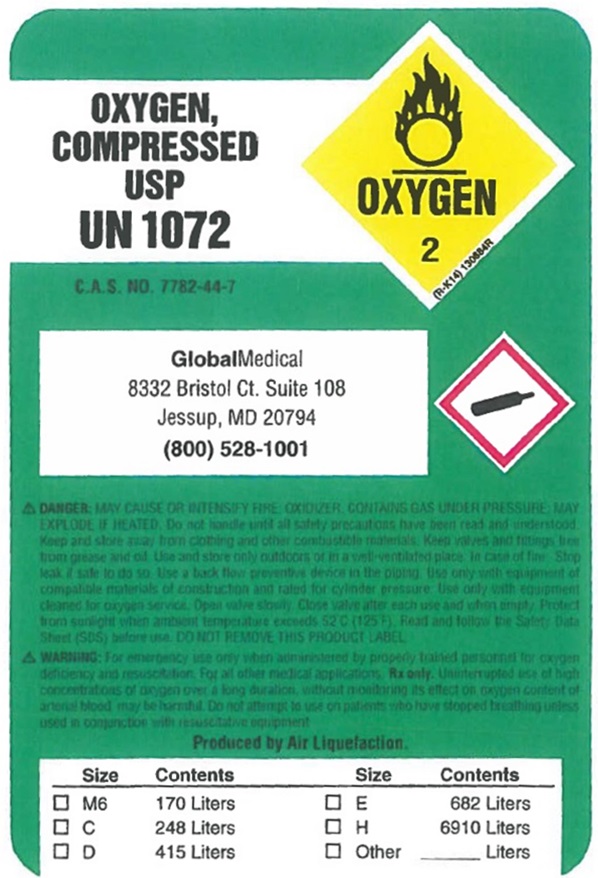 DRUG LABEL: OXYGEN
NDC: 49121-001 | Form: GAS
Manufacturer: Global Medical LLC
Category: prescription | Type: HUMAN PRESCRIPTION DRUG LABEL
Date: 20201215

ACTIVE INGREDIENTS: OXYGEN 99 L/100 L

Oxygen

Oxygen Compressed USP Label

OXYGEN COMPRESSED USP UN 1072 OXYGEN 2

C.A.S. NO. 7782-44-7 GlobalMedical 8332 Bristol Ct. Suite 108 Jessup, MD 20794 800-528-1001

WARNING: HIGH PRESSURE OXIDIZING GAS. VIGOROUSLY ACCELERATES COMBUSTION. NO SMOKING IN THE PRESENCE OF OXYGEN OR A FIRE MAY RESULT.

KEEP OIL AND GREASE AWAY. OPEN VALVE SLOWLY. STORE AND USE WITH ADEQUATE VENTILATION. USE ONLY WITH EQUIPMENT CLEANED FOR OXYGEN SERVICE AND RATED FOR CYLINDER PRESSURE.

USE A BACK FLOW PREVENTATIVE DEVICE IN THE PIPING.

CLOSE VALVE AFTER EACH USE AND WHEN EMPTY. CYLINDER TEMPERATURE SHOULD NOT EXCEED 52 C (125 F)

USE IN ACCORDANCE WITH THE MATERIAL SAFETY DATA SHEET (MSDS)

DO NOT REMOVE THIS PRODUCT LABEL.
WARNING: FOR EMERGENCY USE ONLY WHEN ADMINISTERED BY PROPERLY TRAINED PERSONNEL FOR OXYGEN DEFICIENCY AND RESUSCITATION. FOR ALL OTHER MEDICAL APPLICATIONS Rx ONLY. UNINTERRUPTED USE OF HIGH CONCENTRATIONS OF OXYGEN OVER A LONG DURATION WITHOUT MONITORING ITS EFFECT ON OXYGEN CONTENT OF ARTERIAL BLOOD MAY BE HARMFUL. USE ONLY WITH PRESSURE REDUCING EQUIPMENT AND APPARATUS DESIGNED FOR OXYGEN. DO NOT ATTEMPT TO USE ON PATIENTS WHO HAVE STOPPED BREATHING UNLESS USED IN CONJUNCTION WITH RESUSCITATIVE EQUIPMENT.

PRODUCED BY AIR LIQUEFACTION.

Size Contents

M6 170 Liters

C 248 Liters

D 415 Liters

E 682 Liters

H 6910 Liters

Other ______ Liters